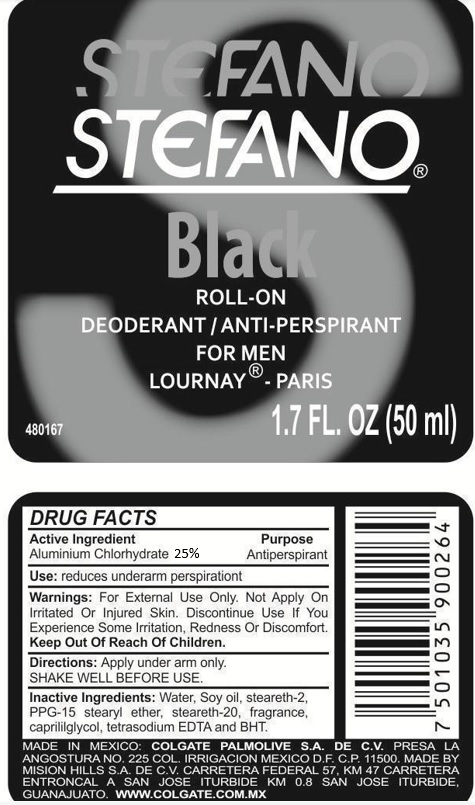 DRUG LABEL: STEFANO
NDC: 51769-999 | Form: STICK
Manufacturer: ALL NATURAL DYNAMICS
Category: otc | Type: HUMAN OTC DRUG LABEL
Date: 20220321

ACTIVE INGREDIENTS: ALUMINUM CHLOROHYDRATE 25 g/100 g
INACTIVE INGREDIENTS: WATER; STEARETH-2; PPG-15 STEARYL ETHER; STEARETH-20; CAPRYLYL GLYCOL; EDETATE SODIUM; BUTYLATED HYDROXYTOLUENE

STEFANO Black

Active Ingredient:

ALUMINUM CHLOROHYDRATE 25%

Purpose:

Antiperspirant

Keep Out Of The Reach Of Children

USE:

reduces underarm persperation.

Warnings:

For External Use Only. Do Not Apply On Irritated Or Injured Skin. Discontinue Use If You Experience Some Irritation, Redness Or Discomfort.

Directions:

Apply under arm only.

SHAKE WELL BEFORE USE.

Inactive Ingredients:

Water, Soy oil, stearth-2, PPG-15 stearyl ether, steareth-20, fragrance, caprylyl glycol, tetrasodium EDTA, and BHT